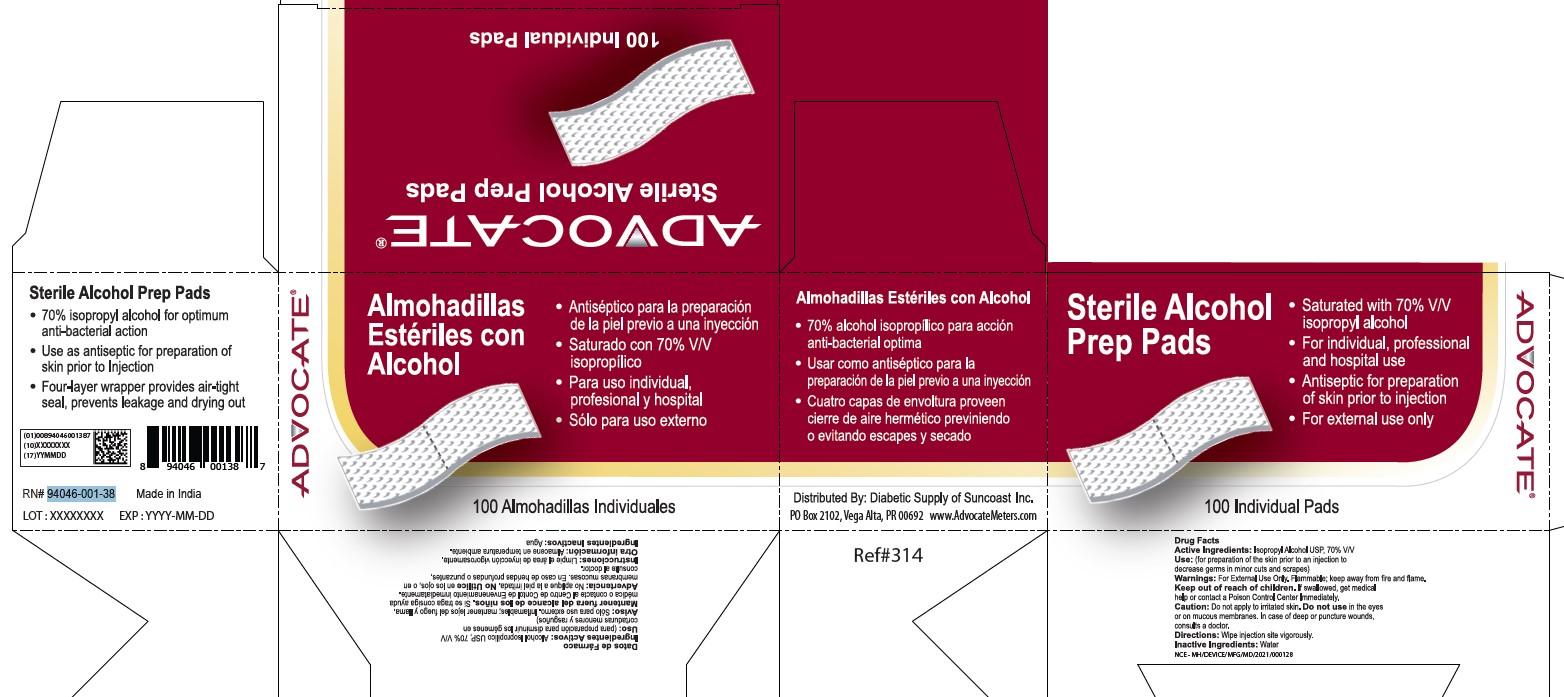 DRUG LABEL: Alcohol Prep Pads
NDC: 60913-045 | Form: SWAB
Manufacturer: Phoenix Healthcare Solutions LLC
Category: otc | Type: HUMAN OTC DRUG LABEL
Date: 20251023

ACTIVE INGREDIENTS: ISOPROPYL ALCOHOL 70 mL/100 mL
INACTIVE INGREDIENTS: WATER

Advocate APP

Active Ingedients

Isopropyl Alcohol 70% V/V

Purpose

Antiseptic

Use

For preparation of the skin prior to injection, to decrease germs in minor cuts and scrapes.

Warnings

For External Use Only. Flammable, keep away from fire and flame.

Keep out of reach of children

If swallowed, get medical help or contact a Poison control centre immediately.

Caution

Do not apply to irritated skin

Do not use

In the eyes, or on mucous membranes. In case of deep or puncture wounds, consult a doctor.

Directions

Wipe injection site vigorously

Other Information

Store at Room Temperature

Inactive Ingredients

Water